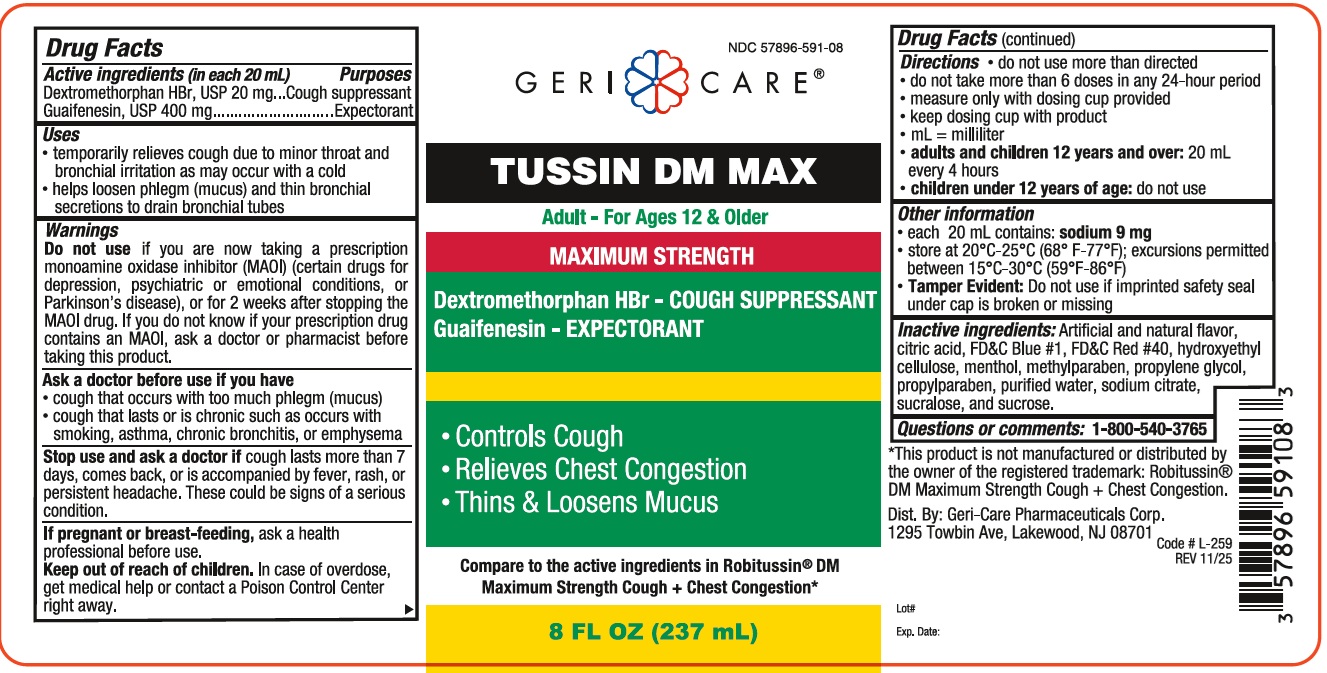 DRUG LABEL: GeriCare Tussin DM Max
NDC: 57896-591 | Form: LIQUID
Manufacturer: GERI-CARE PHARMACEUTICALS, CORP
Category: otc | Type: HUMAN OTC DRUG LABEL
Date: 20251231

ACTIVE INGREDIENTS: DEXTROMETHORPHAN HYDROBROMIDE 20 mg/20 mL; GUAIFENESIN 400 mg/20 mL
INACTIVE INGREDIENTS: ANHYDROUS CITRIC ACID; FD&C RED NO. 40; MENTHOL; METHYLPARABEN; PROPYLENE GLYCOL; PROPYLPARABEN; WATER; SODIUM CITRATE; SUCRALOSE; SUCROSE; HYDROXYETHYL CELLULOSE, UNSPECIFIED; FD&C BLUE NO. 1

GeriCare TussinDMMax 591

ACTIVE INGREDIENT

In each 20 mL

Dextromethorphan HBr- 20 mg

Guaifenesin - 400 mg

Purpose

Cough Suppressant

Expectorant

Uses

- temporarily relieves cough due to minor throat and bronchial irritation
- helps loosen phlegm (mucus)
- helps thin bronchial secretions to make coughs more productive

Warnings

Do not useif you are now taking a prescritpion monamine oxidase inhibitor (MAOI) (certain drugs for depression, psychiatric, or emotional conditions, or Parkinson's diesease), or for 2 weeks after stopping the MAOI drug. If you do not know if your prescirption drug contains an MAOI, aska doctor or pharmacist before taking this product.

Do not useif you have ever had an allergic reaction to any of the ingredients in this product.

Ask a doctor before use if you have

- cough that occurs with too much phlegm (mucus)
- cough that lasts or is chronic such as occurs with smoking, asthma, chronic bronchitis, or emphysema

Stop use and ask a doctor ifcough lasts for more than 7 days, comes back, or is accompanied by fever, rash, or head that lasts. These could be signs of a serious condition.

PREGNANCY OR BREAST FEEDING

If pregnant or breast-feeing,ask a health professional before use.

Keep out of reach of children.In case of overdose, get medical help or contact a Poison Control Cente right away.

Directions:

- do not use more than directed
- do not take more than 6 doses in 24 hours
- measure only with dosing cup provided
- keep dosing cup with product
- mL=mililiter

Age | Dose
Adults and children over 12 years and over | 20 mL every 4 hours
Children under 12 years | do not use

INACTIVE INGREDIENT

Inactive ingredients artificial and natural flavor, citric acid, FD&C Blue #1, FD&C #40, hydroxyethyl cellulose, menthol, methylparaben, propylene glycol, propylparaben, purified water, sodium citrate, sucralose, sucrose.

Questions or comments?1-866-540-3765

RECENT MAJOR CHANGES

fix typos